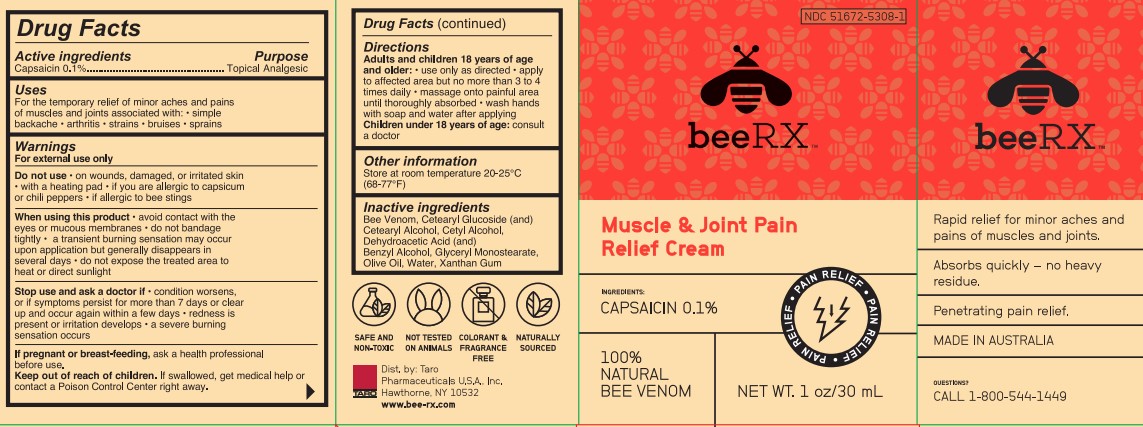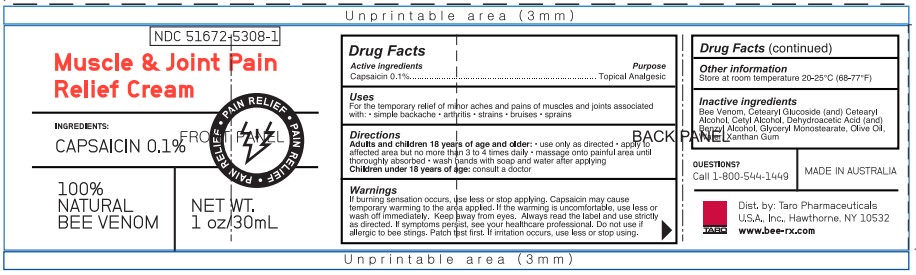 DRUG LABEL: beeRX Muscle and Joint Pain Relief
NDC: 51672-5308 | Form: CREAM
Manufacturer: Taro Pharmaceuticals U.S.A., Inc.
Category: otc | Type: HUMAN OTC DRUG LABEL
Date: 20221005

ACTIVE INGREDIENTS: CAPSAICIN 0.1 g/30 mL
INACTIVE INGREDIENTS: Cetearyl Glucoside; Cetyl Alcohol; Benzyl Alcohol; Invert Sugar; Diglyceryl Monosebacate; Olive Oil; Water; Xanthan Gum; Apis Mellifera Venom; Cetostearyl Alcohol

Drug Facts

Active ingredients | Purpose
Capsaicin 0.1% | Topical Analgesic

Uses

For the temporary relief of minor aches and pains of muscles and joints associated with: ● simple backache ● arthritis ● strains ● bruises ● sprains

Warnings

For external use only

Do not use ● on wounds, damaged, or irritated skin ● with a heating pad ● if you are allergic to capsicum or chili peppers ● if allergic to bee stings

When using this product ● avoid contact with the eyes or mucous membranes ● do not bandage tightly ● a transient burning sensation may occur upon application but generally disappears in several days ● do not expose the treated area to heat or direct sunlight

Stop use and ask a doctor if ● condition worsens, or if symptoms persist for more than 7 days or clear up and occur again within a few days ● redness is present or irritation develops ● a severe burning sensation occurs

If pregnant or breast-feeding, ask a health professional before use.

Keep out of reach of children. If swallowed, get medical help or contact a Poison Control Center fight away.

Directions

Adults and children 18 years of age and older: ● use only as directed ● apply to affected area but no more than 3 to 4 times daily ● massage onto painful area until thoroughly absorbed ● wash hands with soap and water after applying
Children under 18 years of age: consult a doctor

Other Information

Store at room temperature 20-25°C (68-77°F)

Inactive Ingredients

Bee Venon, Ceterayl Glucoside (and) Cetearyl Alcohol, Cetyl Alcohol, Dehydroacetic Acid (and) Benzyl Alcohol, Glyceryl Monostearate, Olive Oil, Water, Xanthan Gum

Questions?

CALL 1-800-544-1449

SAFE AND NON-TOXIC
NOT TESTED ON ANIMALS
COLORANT & FRAGRANCE FREE
NATURALLY SOURCED

Dist. by Taro Pharmaceuticals U.S.A. Inc.
Hawthorne, NY 10532
www.bee-rx.com

PACKAGE LABEL.PRINCIPAL DISPLAY PANEL

NDC 51672-5308-1
beeRXTM
Muscle & Joint Pain
Relief Cream
INGREDIENTS:
CAPSAICIN 0.1%
PAIN RELIEF • PAIN RELIEF • PAIN RELIEF
100%
NATURAL
BEE VENOM
NET WT. 1 oz/30 mL
Rapid relief for minor aches and
pains of muscles and joints.
Absorbs quickly - no heavy
residue.
Penetrating pain relief.
MADE IN AUSTRALIA
Questions?
CALL 1-800-544-1449

SAFE AND
NON-TOXIC
NOT TESTED
ON ANIMALS
COLORANT &
FRAGRANCE
FREE
NATURALLY
SOURCED
Dist. by Taro
Pharmaceuticals U.S.A., Inc.
Hawthorne, NY 10532
www.bee-rx.com

NDC 51672-5308-1
Muscle & Joint Pain
Relief Cream
INGREDIENTS:
CAPSAICIN 0.1%
PAIN RELIEF • PAIN RELIEF • PAIN RELIEF
100%
NATURAL
BEE VENOM
NET WT.
1 oz/30 mL
Dist. by Taro Pharmaceuticals
U.S.A., Inc. Hawthorne, NY 10532
www.bee-rx.com